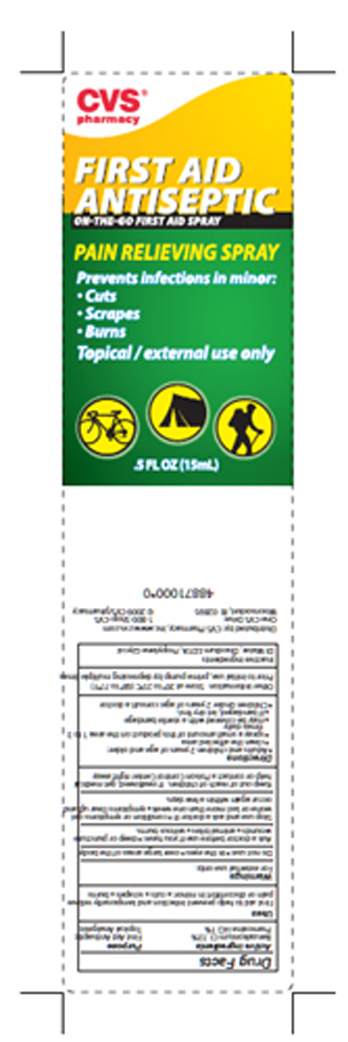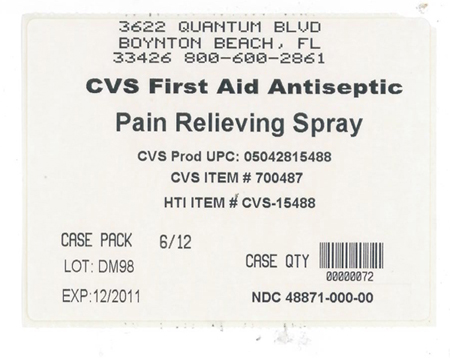 DRUG LABEL: CVS Pharmacy
NDC: 48871-000 | Form: SPRAY
Manufacturer: Health-Tech, Inc.
Category: otc | Type: HUMAN OTC DRUG LABEL
Date: 20100126

ACTIVE INGREDIENTS: Benzalkonium Chloride .195 mL/15 mL; Pramoxine Hydrochloride .15 mL/15 mL
INACTIVE INGREDIENTS: Edetate Disodium; Propylene Glycol; Water

Drug Facts

Active Ingredients

Benzalkonium Chloride

Pramoxine Hydrochloride

Purpose

First Aid Antispetic

Topical Analgesic

Uses

First aid to help prevent infection and temporarily relieve pain or discomfort in minor cuts, scrapes and burns.

Warnings

For external use only.

Do not use

- in the eyes
- overlarge areas of the body

Ask a doctor before use if you have:

- deep or puncture wounds
- animal bites
- serious burns

Stop use and ask a doctor if:

- condition or symptoms get worse or last more than one week
- symptoms clear up and occur again within a few days

Keep out of reach of children.

If swallowed, get medical help or contact a Poison Control Center right away.

Directions

Adults and children 2 years of age and older:

- clean the affected area
- spray a small amount of this product on the area 1 to 3 times daily
- may be covered with a sterile bandage
- if bandaged, let dry first

Children under 2 years of age: consult a doctor

Other information

Store at 20^0 to 25^0 C (68^0 to 77^0 F) Prior to initial use, prime pump by depressing multiple times.

Inactive Ingredients:

DI Water, Edetate Disodium, Propylene Glycol

PACKAGE LABEL

MM1

PACKAGE LABEL

MM3